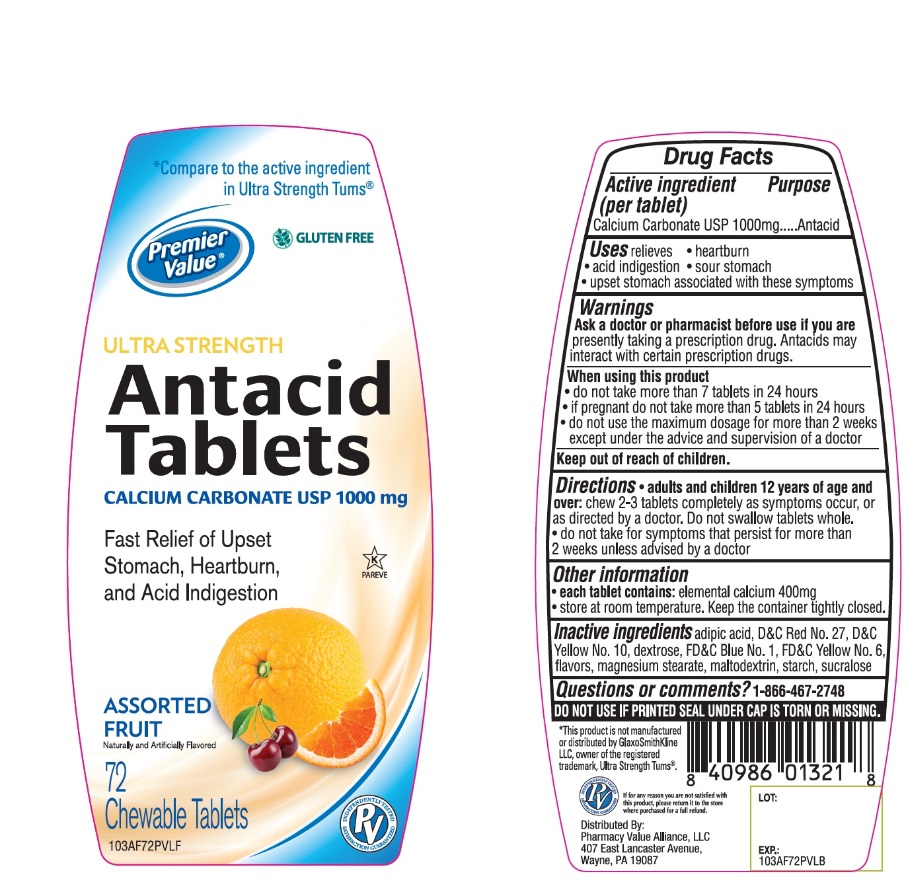 DRUG LABEL: Premier Value Chewable Antacid Ultra Strength
NDC: 68016-669 | Form: TABLET, CHEWABLE
Manufacturer: Chain Drug Consortium
Category: otc | Type: HUMAN OTC DRUG LABEL
Date: 20241025

ACTIVE INGREDIENTS: CALCIUM CARBONATE 500 mg/1 1
INACTIVE INGREDIENTS: ADIPIC ACID; FD&C BLUE NO. 1; DEXTROSE, UNSPECIFIED FORM; MAGNESIUM STEARATE; MALTODEXTRIN; D&C RED NO. 27; STARCH, CORN; SUCRALOSE; FD&C YELLOW NO. 6; D&C YELLOW NO. 10

Drug Facts

Active ingredient

Calcium Carbonate USP 1000mg

Purpose

Antacid

Uses

relieves:

• heartburn

• sour stomach

• acid indigestion

• upset stomach associated with these symptoms

Warnings

Ask a doctor or pharmacist before use if you are taking a prescription drug. Antacids may interact with certain prescription drugs.

When using this product

- do not take more than 7 tablets in 24 hours
- if pregnant do not take more than 5 tablets in 24 hours
- do not use the maximum dosage for more than 2 weeks except under the advice and supervision of a doctor

Directions

- adults and children 12 years of age and over: chew 2-3 tablets as symptoms occur, or as directed by a doctor.
- Do not swallow tablets whole.
- Do not take for symptoms that persist for more than 2 weeks unless advised by a doctor.

Other Information

- each tablet contains: elemental calcium 400mg
- Store at room temperature.
- Keep the container tightly closed

Inactive ingredients

adipic acid, D&C Red No. 27, D&C Yellow No. 10, dextrose, FD&C Blue No. 1, FD&C Yellow No. 6, flavors, magnesium stearate, maltodextrin, , starch, sucralose,

Questions or comments?

1-866-467-2748

Package/Label Principal Display Panel

Compare to the Active Ingredient in Ultra Strength Tums®

Premier Value

GLUTEN FREE

ULTRA STRENGTH

Antacid Tablets

CALCIUM CARBONATE USP 1000 mg

Fast Relief of Heartburn, Acid Indigestion & Upset Stomach

ASSORTED FRUIT

Naturally and Artificially Flavored

72 Chewable Tablets

Distributed by

Pharmacy Value Alliance, LLC

407 East Lancaster Avenue,

Wayne, PA 19087

This product is not manufactured or distributed by GlaxoSmithKline, owner of the registered trademark, Ultra Strength Tums®

Safety sealed: Do not use if printed seal under cap is torn or missing

Premier Value Ultra Strength Assorted Fruit Antacid Tablets

Premier Value Ultra Strength Assorted Fruit Antacid Tablets